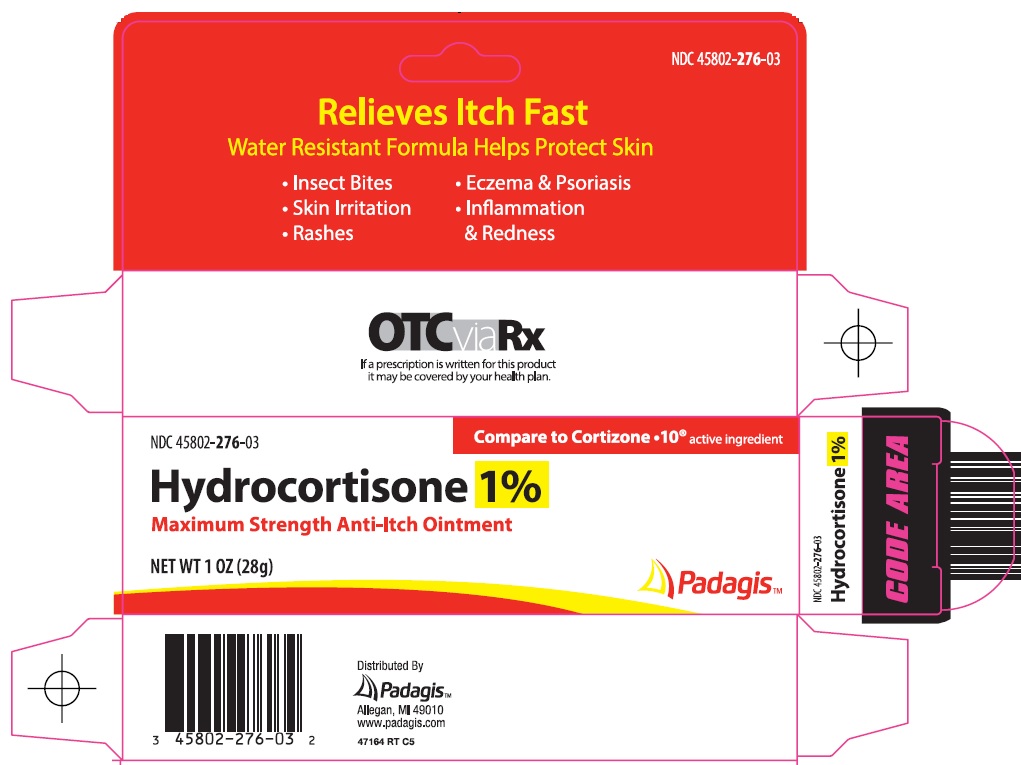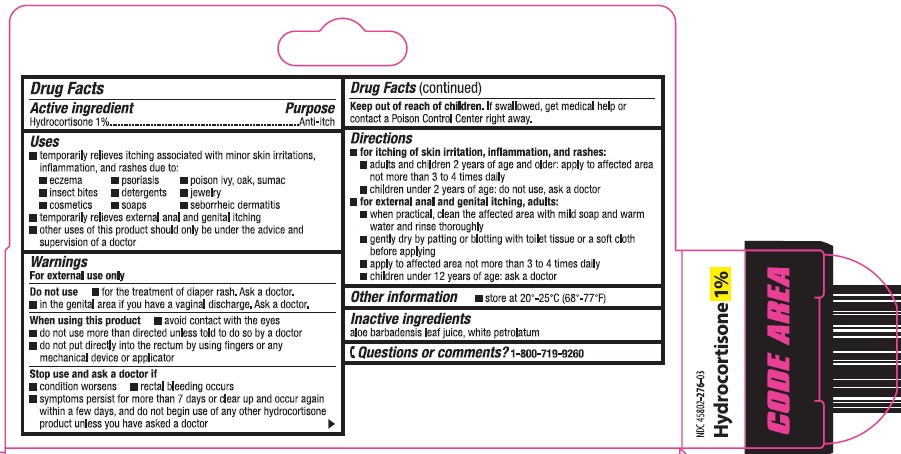 DRUG LABEL: hydrocortisone
NDC: 45802-276 | Form: OINTMENT
Manufacturer: Padagis Israel Pharmaceuticals Ltd
Category: otc | Type: HUMAN OTC DRUG LABEL
Date: 20260114

ACTIVE INGREDIENTS: HYDROCORTISONE 1 g/100 g
INACTIVE INGREDIENTS: ALOE VERA LEAF; PETROLATUM

Hydrocortisone 1% Drug Facts

Active ingredient

Hydrocortisone 1%

Purpose

Anti-itch

Uses

- temporarily relieves itching associated with minor skin irritations, inflammation, and rashes due to:
  - eczema
  - psoriasis
  - poison ivy, oak, sumac
  - insect bites
  - detergents
  - jewelry
  - cosmetics
  - soaps
  - seborrheic dermatitis
- temporarily relieves external anal and genital itching
- other uses of this product should only be under the advice and supervision of a doctor

Warnings

For external use only

Do not use

- for the treatment of diaper rash. Ask a doctor.
- in the genital area if you have a vaginal discharge. Ask a doctor.

When using this product

- avoid contact with the eyes
- do not use more than directed unless told to do so by a doctor
- do not put directly into the rectum by using fingers or any mechanical device or applicator

Stop use and ask a doctor if

- condition worsens
- rectal bleeding occurs
- symptoms persist for more than 7 days or clear up and occur again within a few days, and do not begin use of any other hydrocortisone product unless you have asked a doctor

Keep out of reach of children.

If swallowed, get medical help or contact a Poison Control Center right away.

Directions

- for itching of skin irritation, inflammation, and rashes:
  - adults and children 2 years of age and older: apply to affected area not more than 3 to 4 times daily
  - children under 2 years of age: do not use, ask a doctor
- for external anal and genital itching, adults:
  - when practical, clean the affected area with mild soap and warm water and rinse thoroughly
  - gently dry by patting or blotting with toilet tissue or a soft cloth before applying
  - apply to affected area not more than 3 to 4 times daily
  - children under 12 years of age: ask a doctor

Other information

- store at 20°-25°C (68°-77°F)

Inactive ingredients

aloe barbadensis leaf juice, white petrolatum

Questions or comments?

1-800-719-9260

Principal Display Panel

Relieves Itch Fast

Water Resistant Formula Helps Protect Skin

• Insect Bites

• Skin Irritation

• Rashes

• Eczema & Psoriasis

• Inflammation & Redness

Compare to Cortizone • 10® active ingredient

Hydrocortisone 1%

Maximum Strength Anti-Itch Ointment

NET WT 1 OZ (28 g)

Padagis™